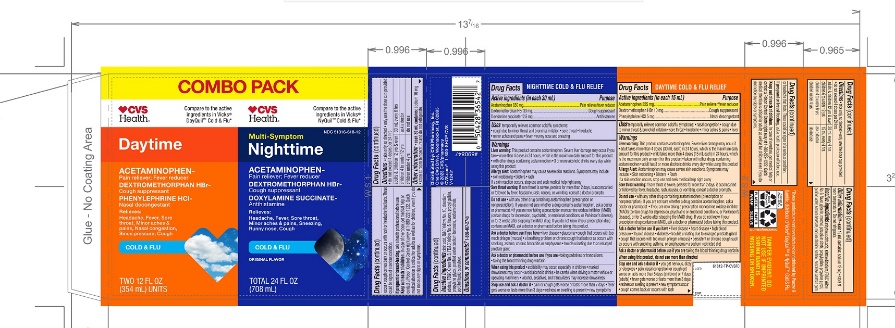 DRUG LABEL: CVS DT and NT Combo Pack

NDC: 51316-618 | Form: KIT | Route: ORAL
Manufacturer: CVS PHARMACY
Category: otc | Type: HUMAN OTC DRUG LABEL
Date: 20251210

ACTIVE INGREDIENTS: ACETAMINOPHEN 325 mg/15 mL; DEXTROMETHORPHAN HYDROBROMIDE 10 mg/15 mL; PHENYLEPHRINE HYDROCHLORIDE 5 mg/15 mL; ACETAMINOPHEN 650 mg/30 mL; DEXTROMETHORPHAN HYDROBROMIDE 30 mg/30 mL; DOXYLAMINE SUCCINATE 12.5 mg/30 mL
INACTIVE INGREDIENTS: ANHYDROUS CITRIC ACID; EDETATE DISODIUM; FD&C YELLOW NO. 6; GLYCERIN; MENTHOL, UNSPECIFIED FORM; POTASSIUM CITRATE; PROPYL GALLATE; PROPYLENE GLYCOL; WATER; SODIUM BENZOATE; SODIUM CHLORIDE; SORBITOL; SUCRALOSE; XANTHAN GUM; ANHYDROUS CITRIC ACID; D&C YELLOW NO. 10; EDETATE DISODIUM; FD&C GREEN NO. 3; FD&C YELLOW NO. 6; PROPYL GALLATE; PROPYLENE GLYCOL; WATER; SODIUM BENZOATE; SODIUM CITRATE, UNSPECIFIED FORM; SORBITOL; SUCRALOSE

CVS DT & NT Combo Pack Cold & Flu

CVS DayTime Cold & Flu Relief

Active ingredients (in each 15 mL)

Acetaminophen 325 mg
Dextromethorphan HBr 10 mg
Phenylephrine HCl 5 mg

Purpose

Pain reliever/Fever reducer
Cough suppressant
Nasal decongestant

Uses

- temporarily relieves common cold/flu symptoms:
- nasal congestion
- cough due to minor throat & bronchial irritation
- minor aches & pains
- headache
- fever
- sore throat

Warnings

Liver warning

This product contains acetaminophen.

Severe liver damage may occur if you take

- adult takes more than 4 doses (30 mL each) in 24 hours, which is the maximum daily amount for this product
- child takes more than 4 doses (15 mL each) in 24 hours, which is the maximum daily amount for this product
- taken with other drugs containing acetaminophen
- adult has 3 or more alcoholic drinks every day while using this product

Allergy Alert:

Acetaminophen may cause severe skin reactions. Symptoms may include:

- Skin reddening
- Blisters
- Rash

If a skin reaction occurs, stop use and seek medical help right away

Sore throat warning:

If sore throat is severe, persists for more than 2 days, is accompanied or followed by fever, headache, rash, nausea, or vomiting, consult a doctor promptly.

Do not use

- with any other drug containing acetaminophen (prescription or nonprescription). If you are not sure whether a drug contains acetaminophen, ask a doctor or pharmacist.
- if you are now taking a prescription monoamine oxidase inhibitor (MAOI) (certain drugs for depression, psychiatric or emotional conditions, or Parkinson's disease), or for 2 weeks after stopping the MAOI drug. If you do not know if your prescription drug contains an MAOI, ask a doctor or pharmacist before taking this product.

Ask a doctor before use if you have

- Liver disease
- Heart disease
- High blood pressure
- Thyroid disease
- Diabetes
- Trouble urinating due to enlarged prostate gland
- Cough that occurs with too much phlegm (mucus)
- Persistent or chronic cough such as occurs with smoking, asthma, or emphysema
- A sodium-restricted diet

Ask a doctor or pharmacist before use if you aretaking the blood thinning drug warfarin.

When using this product, do not use more than directed.

Stop use and ask a doctor if

- you get nervous, dizzy or sleepless
- pain, nasal congestion, or cough gets worse or lasts more than 5 days (children) or 7 days (adult)
- fever gets worse or lasts more than 3 days
- redness or swelling is present
- new symptoms occur
- cough comes back or occurs with rash or headache that lasts.
  These could be signs of a serious condition.

PREGNANCY OR BREAST FEEDING

If pregnant or breast-feeding,ask a health professional before use.

Keep out of reach of children.In case of overdose, get medical help or contact a Poison Control Center right away. Quick medical attention is critical for adults as well as for children even if you do not notice any signs or symptoms.

Directions

- take only as directed
- Only use the dose cup provided
- do not exceed 4 doses per 24 hrs

adults & children 12 yrs & over | 30 mL every 4 hours
Children 6 to under 12 yrs | 15 mL every 4 hours
children 4 to under 12 yrs | ask a doctor
children under 4 yrs | do not use

Other information

each 15 mL contains:

- sodium 42 mg
- store at room temperature
- Do not refrigerate.

Inactive ingredients

Anhydrous citric acid, disodium edetate, FD&C Yellow No. 6, flavor, glycerin, menthol, potassium citrate, propyl gallate, purified water, sodium benzoate, sodium chloride, sorbitol, sucralose, xanthan gum

Questions?

1-866-467-2748

CVSNIGHTTIME COLD & FLU RELIEF

Active ingredients (in each 30 mL)

Acetaminophen 650 mg
Dextromethorphan HBr 30 mg
Doxylamine succinate 12.5 mg

Purpose

Pain reliever/Fever reducer
Cough suppressant
Antihistamine

Uses

temporarily relieves common cold/flu symptoms:

- cough due to minor throat & bronchial irritation
- minor aches & pains
- headache
- fever
- sore throat
- runny nose & sneezing

Warnings

Liver warning

This product contains acetaminophen.

Severe liver damage may occur if you take

- more than 4 doses in 24 hours, which is the maximum daily amount for this product
- taken with other drugs containing acetaminophen
- 3 or more alcoholic drinks every day while using this product

Allergy Alert:

acetaminophen may cause severe skin reactions.
Symptoms may include:

- Skin reddening
- Blisters
- Rash

If a skin reaction occurs, stop use and seek medical help right away

Sore throat warning:

If sore throat is severe, persists for more than 2 days, is accompanied or followed by fever, headache, rash, nausea, or vomiting, consult a doctor promptly.

Do not use

- with any other drug containing acetaminophen (prescription or nonprescription). If you are not sure whether a drug contains acetaminophen, ask a doctor or pharmacist.
- if you are now taking a prescription monoamine oxidase inhibitor (MAOI) (certain drugs for depression, psychiatric or emotional conditions, or Parkinson's disease), or for 2 weeks after stopping the MAOI drug. If you do not know if your prescription drug contains an MAOI, ask a doctor or pharmacist before taking this product.

Ask a doctor before use if you have

- Liver disease
- glaucoma
- Trouble urinating due to enlarged prostate gland
- Cough that occurs with too much phlegm (mucus)
- A breathing problem or chronic cough such as occurs with smoking, asthma, or emphysema

Ask a doctor or pharmacist before use if you are

- Taking sedatives or tranquilizers
- Taking the blood thinning drug warfarin

When using this product

- excitability may occur, especially in children
- marked drowsiness may occur
- avoid alcoholic drinks
- be careful when driving a motor vehicle or operating machinery
- alcohol, sedatives & tranquilizers may increase drowsiness

Stop use and ask a doctor if

- pain, or cough gets worse or lasts more than 7 days
- fever gets worse or lasts more than 3 days
- redness or swelling is present
- new symptoms occur
- cough comes back or occurs with rash or headache that lasts.
  These could be signs of a serious condition.

PREGNANCY OR BREAST FEEDING

If pregnant or breast-feeding,ask a health professional before use.

Keep out of reach of children.In case of overdose, get medical help or contact a Poison Control Center right away. Quick medical attention is critical for adults as well as for children even if you do not notice any signs or symptoms.

Directions

- take only as directed
- Only use the dose cup provided
- do not exceed 4 doses per 24 hrs

adults & children 12 yrs & over | 30 mL every 4 hours
children 4 to under 12 yrs | ask a doctor
children under 4 yrs | do not use

Other information

- each 30 mL contains: sodium 16 mg
- Store at room temperature
- Do not refrigerate

Inactive ingredients

Citric acid, D&C Yellow No. 10, disodium edetate, FD&C Green No.3, FD&C Yellow no 6, flavor, propyl gallate, propylene glycol, purified water, sodium benzoate, sodium citrate, sorbitol, sucralose

Questions?

1-866-467-2748

Distributed By:

PRINCIPAL DISPLAY PANEL - Kit Carton

Compare to the active ingredients in Vicks®DayQuil™ Cold & Flu*

NDC# 51316-618-12

DayTime

Cold & Flu

Relief

Acetaminophen,Dextromethorphan HBr,

Phenylephrine HCl

- Headache, Fever, Sore Throat, Minor Aches & Pains
- Nasal Congestion & Sinus Pressure
- Cough

Compare to the active ingredients in Vicks®NyQuil™ Cold & Flu*

NightTime

Cold & Flu

Relief

Acetaminophen,Dextromethorphan HBr

Dextromethorphan HBr

- headache, Fever, Sore Throat,
- Minor Aches & Pains
- Sneezing, Runny Nose
- Cough

Original Flavor

Tamper Evident: Do not use if imprinted shrink band is missing or broken.

TWO BOTTLES, 12 FL OZ (354 mL) each; TOTAL 24 FL OZ (708 mL)

*These product is not manufactured or distributed by Procter & Gamble, distributor of Vicks®Dayquil™ and Vicks® Nyquil™ Cold & flu.